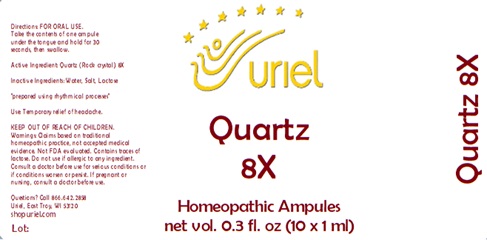 DRUG LABEL: Quartz 8
NDC: 48951-8109 | Form: LIQUID
Manufacturer: Uriel Pharmacy Inc.
Category: homeopathic | Type: HUMAN OTC DRUG LABEL
Date: 20240426

ACTIVE INGREDIENTS: SILICON DIOXIDE 8 [hp_X]/1 mL
INACTIVE INGREDIENTS: WATER; SODIUM CHLORIDE; LACTOSE, UNSPECIFIED FORM

Quartz 8

INDICATIONS AND USAGE

Directions: FOR ORAL USE.

DOSAGE AND ADMINISTRATION

Take the contents of one ampule under the tongue and hold for 30 seconds, then swallow.

Active Ingredient: Quartz (Rock crystal) 8X

Inactive Ingredients: Water, Salt, Lactose

"prepared using rhythmical processes"

PURPOSE

Use: Temporary relief of headache.

KEEP OUT OF REACH OF CHILDREN.

WARNINGS

Warnings: Claims based on traditional homeopathic practice, not accepted medical evidence. Not FDA evaluated. Contains traces of lactose. Do not use if allergic to any ingredient. Consult a doctor before use for serious conditions or if conditions worsen or persist. If pregnant or nursing, consult a doctor before use.

QUESTIONS

Questions? Call 866.642.2858 Uriel, East Troy, WI 53120 shopuriel.com Lot: